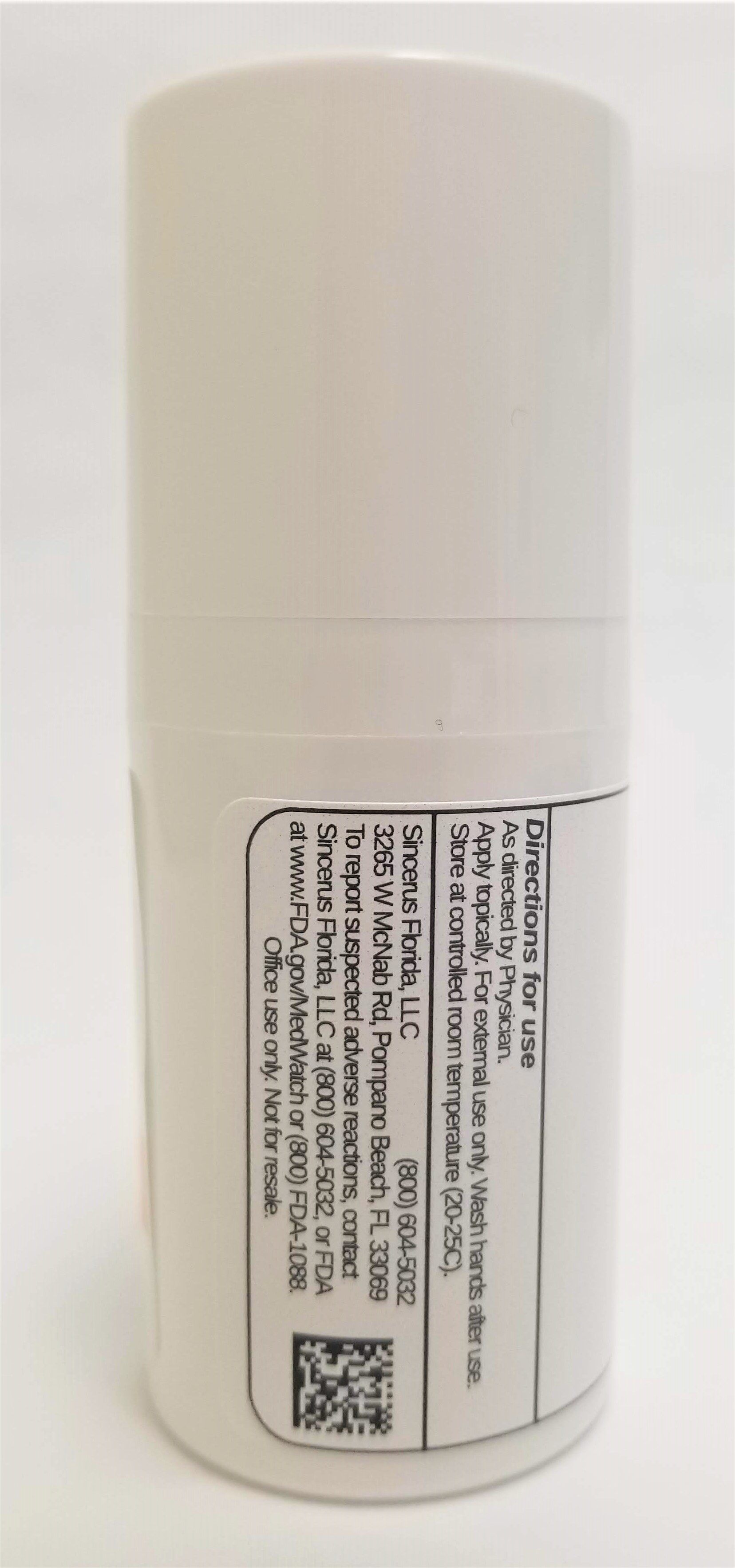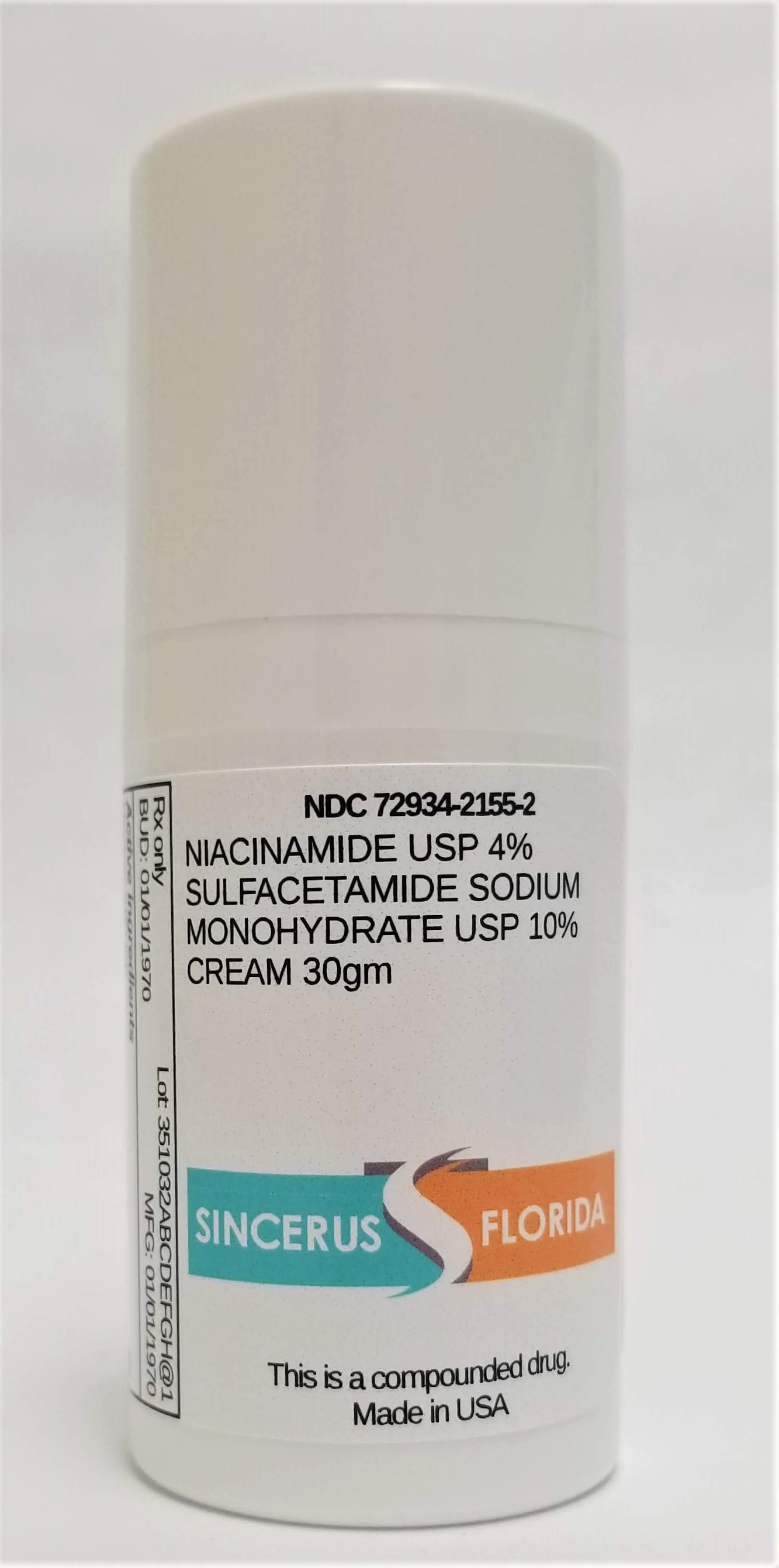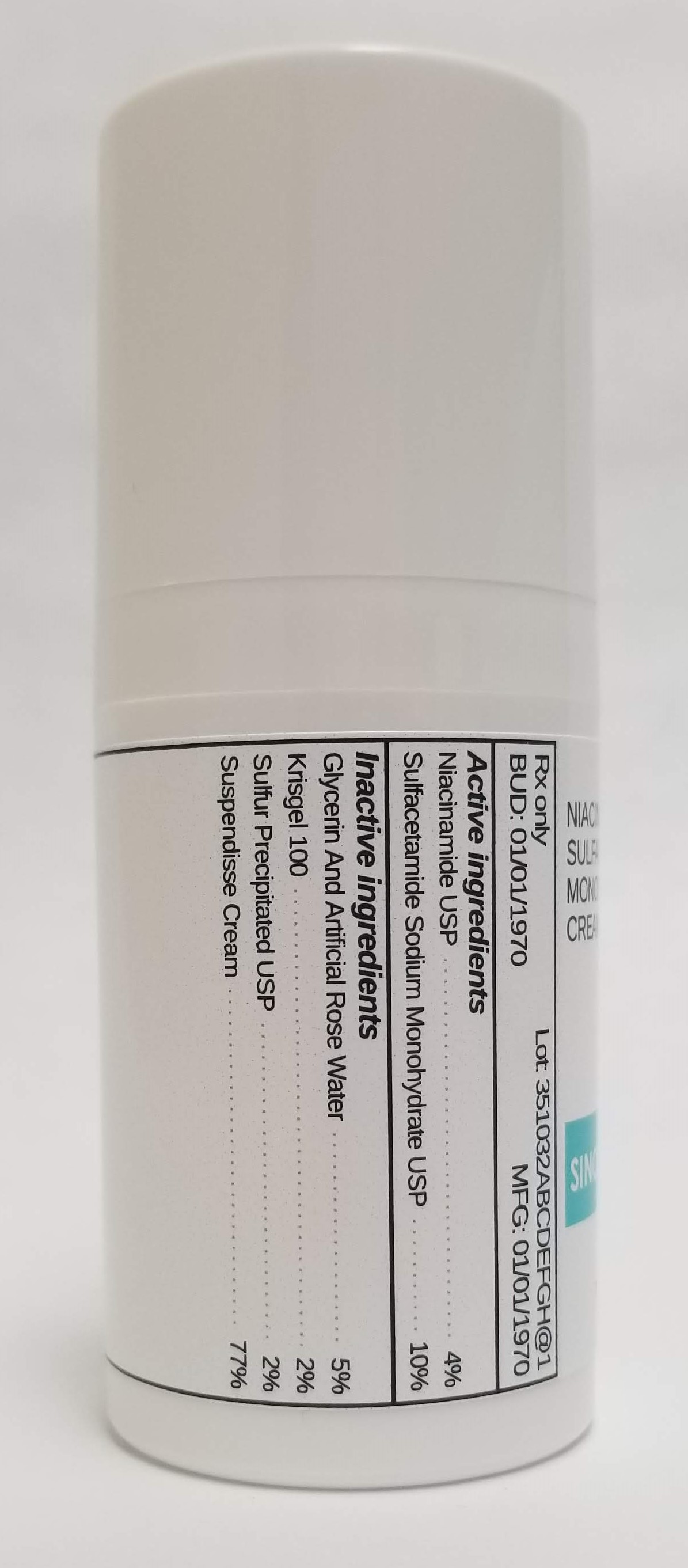 DRUG LABEL: NIACINAMIDE 4% / SODIUM SULFACETAMIDE MONOHYDRATE 10% / SULFUR PRECIPITATED 2%
NDC: 72934-2155 | Form: CREAM
Manufacturer: Sincerus Florida, LLC
Category: prescription | Type: HUMAN PRESCRIPTION DRUG LABEL
Date: 20190514

ACTIVE INGREDIENTS: SULFACETAMIDE SODIUM 10 g/100 g; NIACINAMIDE 4 g/100 g

NIACINAMIDE 4% / SODIUM SULFACETAMIDE MONOHYDRATE 10% / SULFUR PRECIPITATED 2%